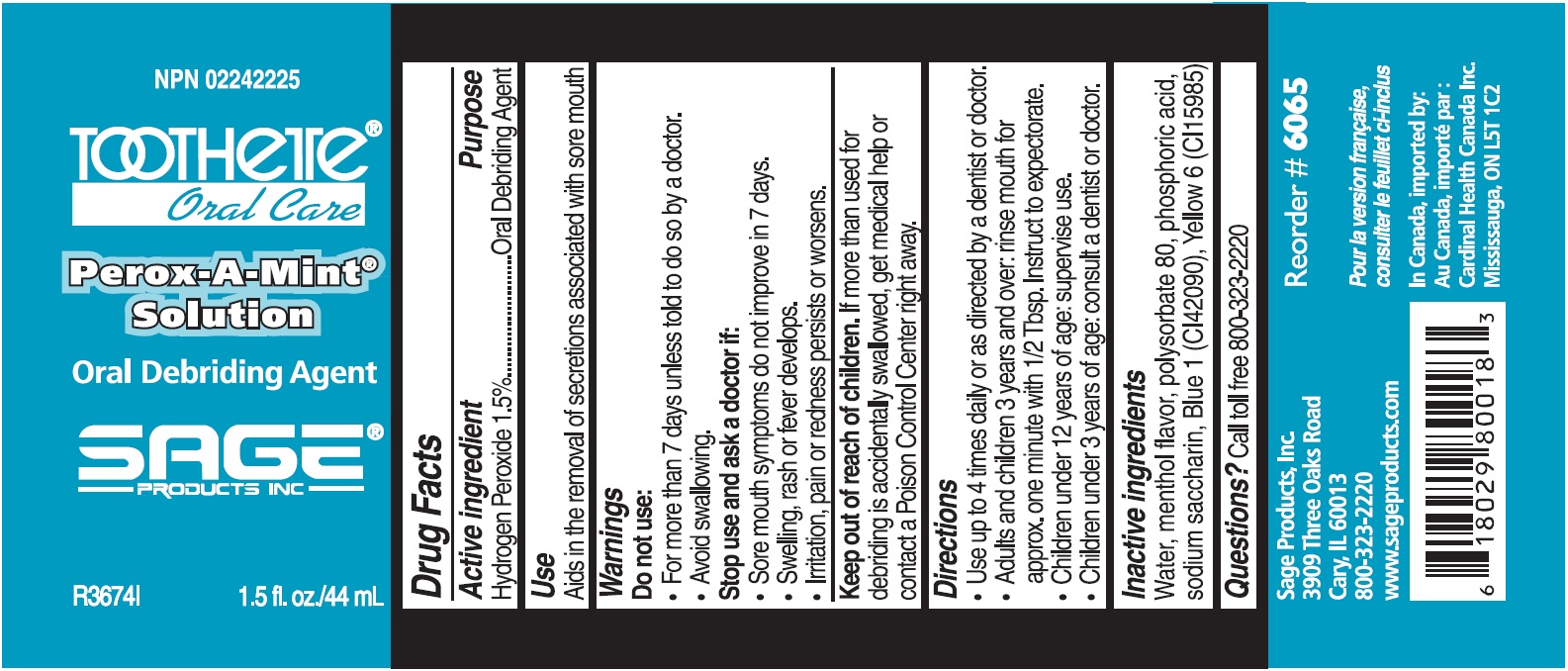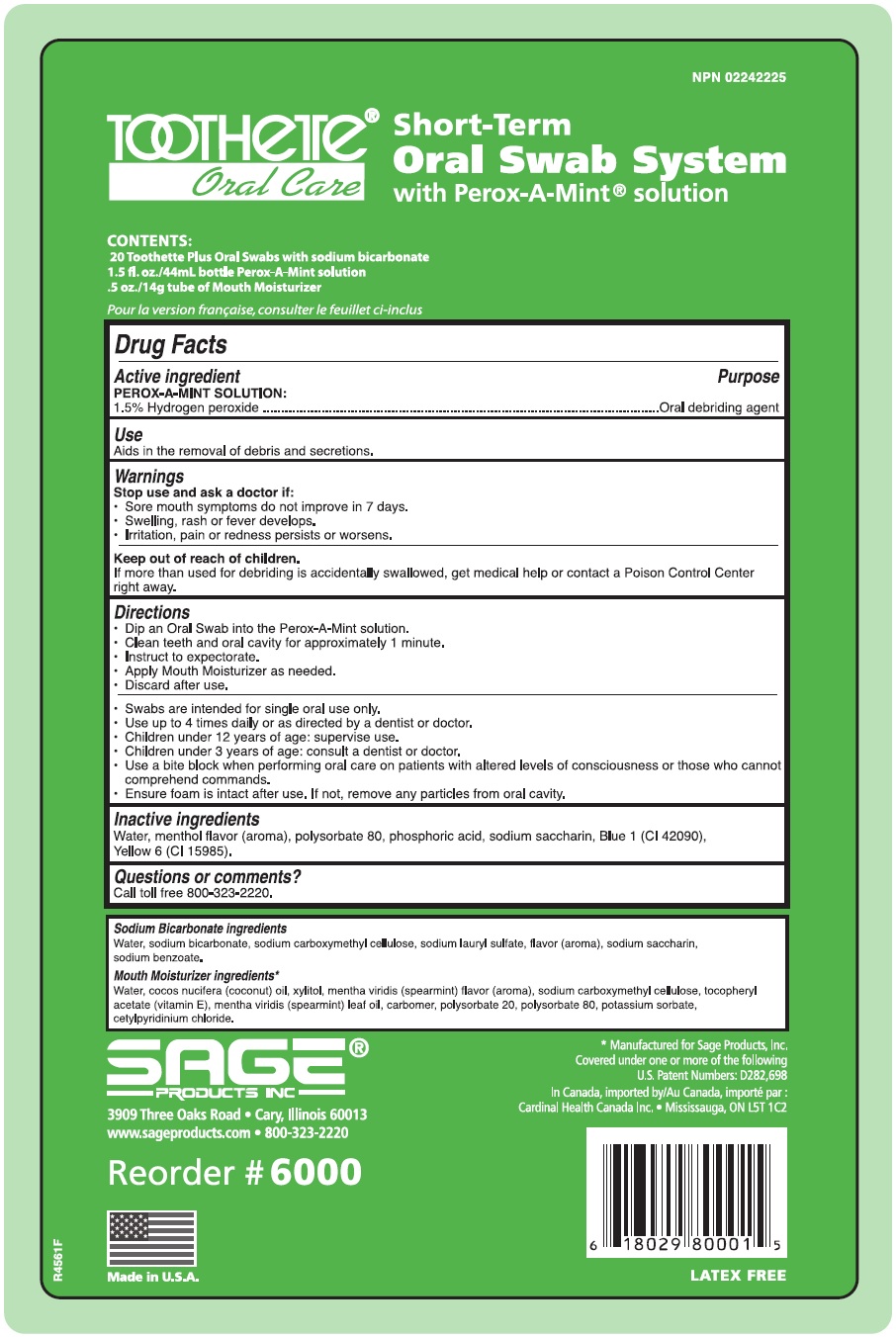 DRUG LABEL: Short Term Oral Swab System
NDC: 53462-201 | Form: KIT | Route: BUCCAL
Manufacturer: Sage Products LLC
Category: otc | Type: HUMAN OTC DRUG LABEL
Date: 20190117

ACTIVE INGREDIENTS: HYDROGEN PEROXIDE 15 mg/1 mL
INACTIVE INGREDIENTS: WATER; PHOSPHORIC ACID; POLYSORBATE 80; SACCHARIN SODIUM; FD&C BLUE NO. 1; FD&C YELLOW NO. 6

Short Term Oral Swab System

Drug Facts

Active Ingredient | Purpose
PEROX-A-MINT SOLUTION:
1.5% Hydrogen peroxide | Oral debriding agent

Use

Aids in the removal of secretions associated with sore mouth

Warnings

Do not use:

- For more than 7 days unless told to do so by a doctor.
- Avoid Swallowing.

Stop use and ask a doctor if:

- Sore mouth symptoms do not improve in 7 days.
- Swelling, rash or fever develops.
- Irritation, pain or redness persists or worsens.

Keep out of reach of children.

If more than used for debriding is accidentally swallowed, get medical help or contact a Poison Control Center right away.

Directions

Perox-A-Mint

- Use up to 4 times daily or as directed by a dentist or doctor.
- Adults and children 3 years and over: rinse mouth for approx. one minute with 1/2 Tbsp. Instruct to expectorate.
- Children under 12 years of age: supervise use.
- Children under 3 years of age: consult a dentist or doctor.

Oral Swab System

- Dip an Oral Swab into the Perox-A-Mint solution.
- Clean teeth and oral cavity for approximately one minute.
- Instruct to expectorate.
- Apply Mouth Moisturizer as needed.
- Discard after use.
- Swabs are intended for single oral use only.
- Use up to 4 times daily or as directed by a dentist or doctor.
- Children under 12 years of age should be supervised in the use of this product.
- Children under 3 years of age: consult a dentist or doctor.
- Use a bite block when performing oral care on patients with altered levels of consciousness or those who cannot comprehend commands.
- Ensure foam is intact after use. If not, remove any particles from oral cavity.

Inactive Ingredients

Water, menthol flavor, polysorbate 80, phosphoric acid, sodium saccharin, Blue 1 (CI42090), Yellow 6 (CI15985)

Questions

Call toll free 800-323-2220

MADE IN U.S.A.

NOT MADE WITH NATURAL RUBBER LATEX